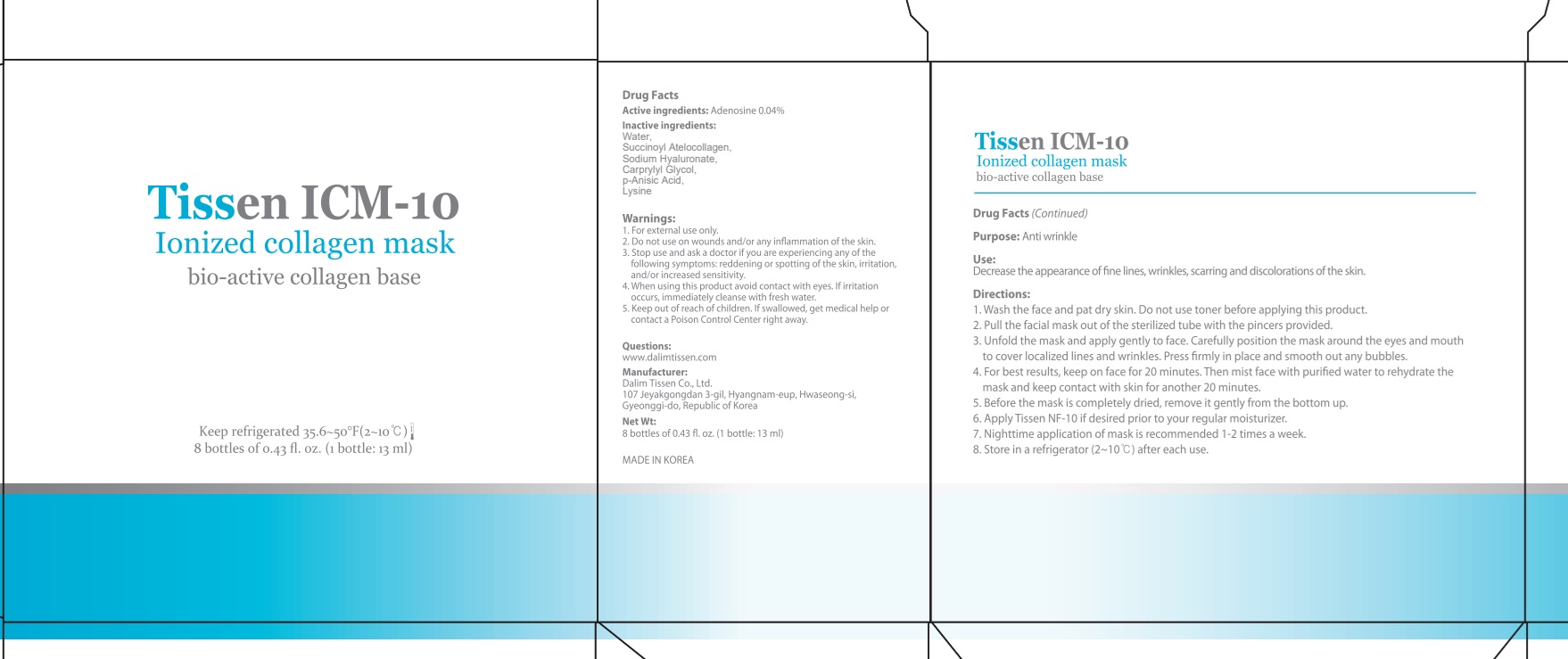 DRUG LABEL: Tissen ICM 10
NDC: 42491-1200 | Form: LIQUID
Manufacturer: Dalim Tissen
Category: otc | Type: HUMAN OTC DRUG LABEL
Date: 20241125

ACTIVE INGREDIENTS: ADENOSINE 0.005 g/13 mL
INACTIVE INGREDIENTS: WATER; HYALURONATE SODIUM

ACTIVE INGREDIENT

Active ingredients: Adenosine 0.04%

INACTIVE INGREDIENT

Inactive ingredients:

Water, Succinoyl atelocollagen, Sodium hyaluronate, Methyl paraben, Propyl paraben, Lysine, L-

PURPOSE

Purpose: Anti wrinkle

WARNINGS

1. For external use only.
2. Do not use on wounds and/or any inflammation of the skin.
3. Stop use and ask a doctor if you are experiencing any of the following symptoms: reddening or spotting of the skin, irritation, and/or increased sensitivity.
4. When using this product avoid contact with eyes. If irritation occurs, immediately cleanse with fresh water.
5. Keep out of reach of children. If swallowed, get medical help or contact a Poison Control Center right away.

KEEP OUT OF REACH OF CHILDREN

Uses

Uses: Decrease the appearance of fine lines, wrinkles, scarring and discolorations of the skin

Directions

1. Wash the face and pat dry skin. Do not use toner before applying this product.
2. Pull the facial mask out of the sterilized tube with the pincers provided.
3. Unfold the mask and apply gently to face. Carefully position the mask around the eyes and mouth to cover localized lines and wrinkles. Press firmly in place and smooth out any bubbles.
4. For best results, keep on face for 20 minutes. Then mist face with purified water to rehydrate the mask and keep contact with skin for another 20 minutes.
5. Before the mask is completely dried, remove it gently from the bottom up.
6. Apply Tissen NF-10 if desired prior to your regular moisturizer.
7. Nighttime application of mask is recommended 1-2 times a week.
8. Store in a refrigerator (2-15℃) after each use